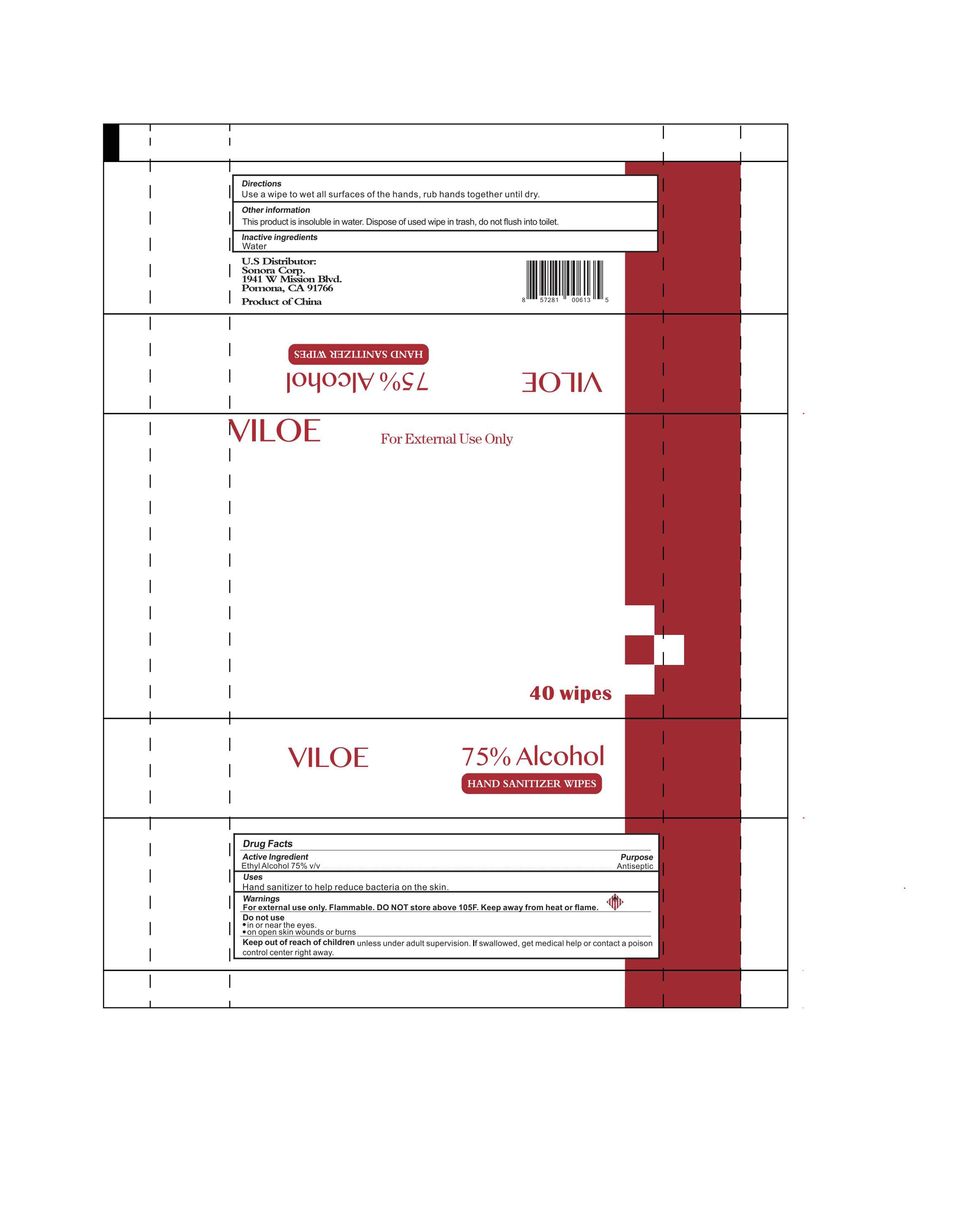 DRUG LABEL: VILOE
NDC: 75622-222 | Form: CLOTH
Manufacturer: Henan Yeesain Health Technology Co., Ltd.	
Category: otc | Type: HUMAN OTC DRUG LABEL
Date: 20231108

ACTIVE INGREDIENTS: ALCOHOL 0.75 mL/1 1
INACTIVE INGREDIENTS: WATER

Henan-Sorona Sanitizing Wipes

Active Ingredient(s)

Alcohol 75% v/v. Purpose: Antiseptic

Purpose

Antiseptic

Use

Hand Sanitizer to help reduce bacteria on the skin.

Warnings

For external use only. Do not store above 105F. Keep away from heat or flame

Do not use

- in or near the eyes.
- on open skin wounds or burns

Keep out of reach of children unless under adult supervision. If swallowed, get medical help or contact a poison control center right away

Directions

Use a wipe to wet all surfaces of the hands, rub hands together until its dry.

Other information

This product is insoluble in water. Dispose of used wipes in the trash, do not flush into the toilet.

Inactive ingredients

Purified Water

Package Label - Principal Display Panel

40 PCS NDC: 75622-222-40